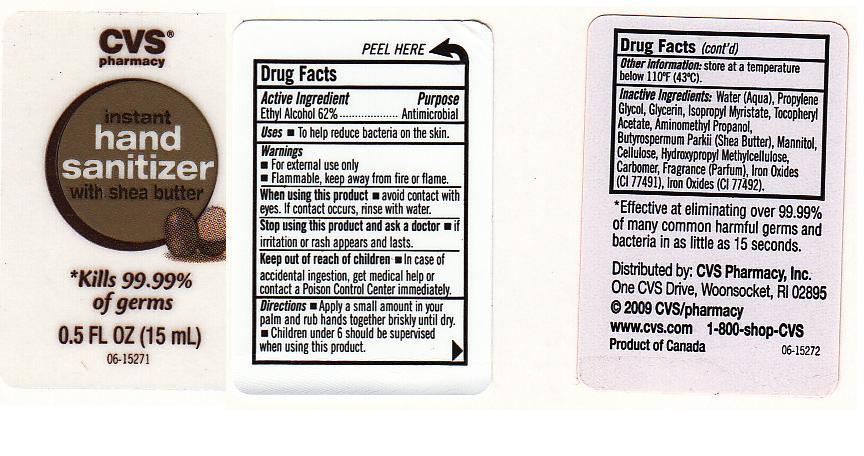 DRUG LABEL: INSTANT HAND SANITIZER
NDC: 59779-224 | Form: GEL
Manufacturer: CVS PHARMACY
Category: otc | Type: HUMAN OTC DRUG LABEL
Date: 20110131

ACTIVE INGREDIENTS: ALCOHOL 62 mL/100 mL
INACTIVE INGREDIENTS: WATER; PROPYLENE GLYCOL; GLYCERIN; ISOPROPYL MYRISTATE; .ALPHA.-TOCOPHEROL ACETATE, D-; AMINOMETHYLPROPANOL; SHEA BUTTER; MANNITOL; POWDERED CELLULOSE; HYPROMELLOSES; CARBOMER 934; FERRIC OXIDE RED; FERRIC OXIDE YELLOW

DRUG FACTS

ACTIVE INGREDIENT

ETHYL ALCOHOL 62%

PURPOSE

ANTIMICROBIAL

USES

TO HELP REDUCE BACTERIA ON THE SKIN.

WARNINGS

FOR EXTERNAL USE ONLY-HANDS.

FLAMMABLE. KEEP AWAY FROM FIRE OR FLAME.

WHEN USING THIS PRODUCT

AVOID CONTACT WITH EYES. IF CONTACT OCCURS, RINSE WITH WATER.

STOP USING AND ASK A DOCTOR

IF IRRITATION OR RASH APPEARS AND LASTS.

KEEP OUT OF REACH OF CHILDREN

IN CASE OF ACCIDENTAL INGESTION, GET MEDICAL HELP OR CONTACT A POISON CONTROL CENTER IMMEDIATELY.

DIRECTIONS

APPLY A SMALL AMOUNT IN YOUR PALM AND RUB HANDS TOGETHER BRISKLY UNTIL DRY. CHILDREN UNDER 6 SHOULD BE SUPERVISED WHEN USING THIS PRODUCT.

OTHER INFORMATION

STORE AT A TEMPERATURE BELOW 110 DEGREES FAHRENHEIT (43 DEGREES CELCIUS).

INACTIVE INGREDIENTS

WATER, PROPYLENE GLYCOL, GLYCERIN, ISOPROPYL MYRISTATE, TOCOPHERYL ACETATE, AMINOMETHYL PROPANOL, BUTYROSPERMUM PARKII (SHEA BUTTER), MANNITOL, CELLULOSE, HYDROXYPROPYL METHYLCELLULOSE, CARBOMER, FRAGRANCE, IRON OXIDES (CI 77491), IRON OXIDES (CI 77492).